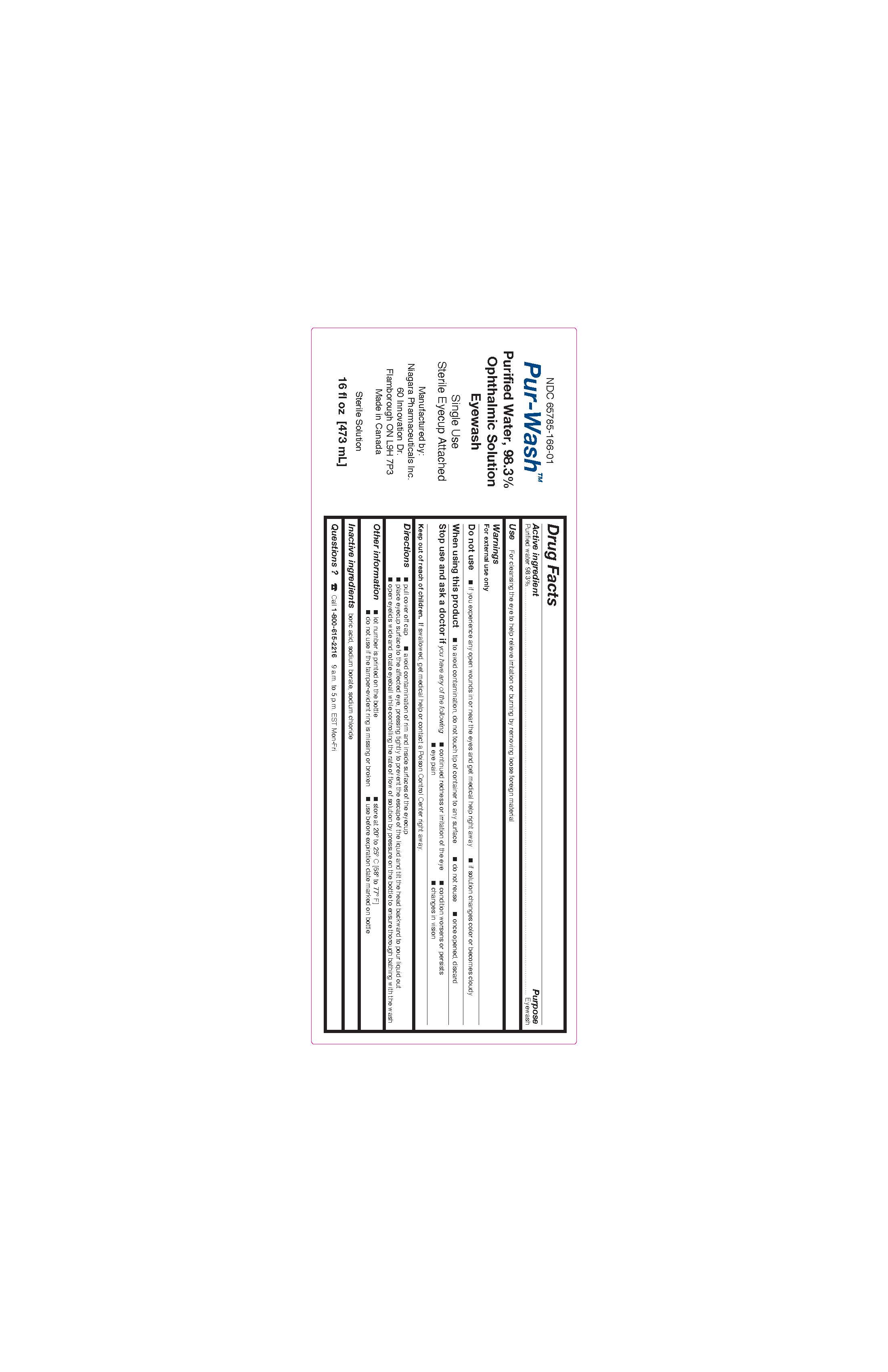 DRUG LABEL: PUR-WASH
NDC: 65785-166 | Form: SOLUTION
Manufacturer: Niagara Pharmaceuticals Inc.
Category: otc | Type: HUMAN OTC DRUG LABEL
Date: 20251124

ACTIVE INGREDIENTS: WATER 929 g/946 mL
INACTIVE INGREDIENTS: BORIC ACID; SODIUM CHLORIDE; SODIUM BORATE

Pur-Wash

Drug Facts

Active ingredient

Purified water 98.3%

Purpose

Eyewash

Use

For cleansing the eye to help relieve irritation or burning by removing loose foreign material

Warnings

For external use only

Do not use

- if you experience any open wounds in or near the eyes and obtain immediate medical treatment
- if solution changes color or becomes cloudy

When using this product

- to avoid contamination, do not touch tip of container to any surface
- do not reuse
- once opened, discard

Stop use and ask a doctor ifyou have any of the following

- continued redness or irritation of the eye
- condition worsens or persists
- eye pain
- changes in vision

Keep out of reach of children.

If swallowed, get medical help or contact a Poison Control Center right away.

Directions

• pull cover off cap

• avoid contamination of rim and inside surfaces of the eyecup

• place eyecup surface to the affected eye, pressing tightly to prevent the escape of the liquid and tilt the head backward

• open eyelids wide and rotate eyeball while controlling the rate of flow of solution by pressure on the bottle to ensure thorough bathing with the wash

Other information

- lot number is printed on the bottle
- store at 20° to 25° C [68° to 77° F]
- do not use if tamper evident ring is broken
- use before expiration date marked on bottle

Inactive ingredients

boric acid, sodium borate, sodium chloride

Questions ?

☎ Call 905 690-6277 9 a.m. to 5 p.m. EST Mon-Fri

Manufactured by:
Niagara Pharmaceuticals Inc.
60 Innovation Dr.
Flamborough ON L9H 7P3